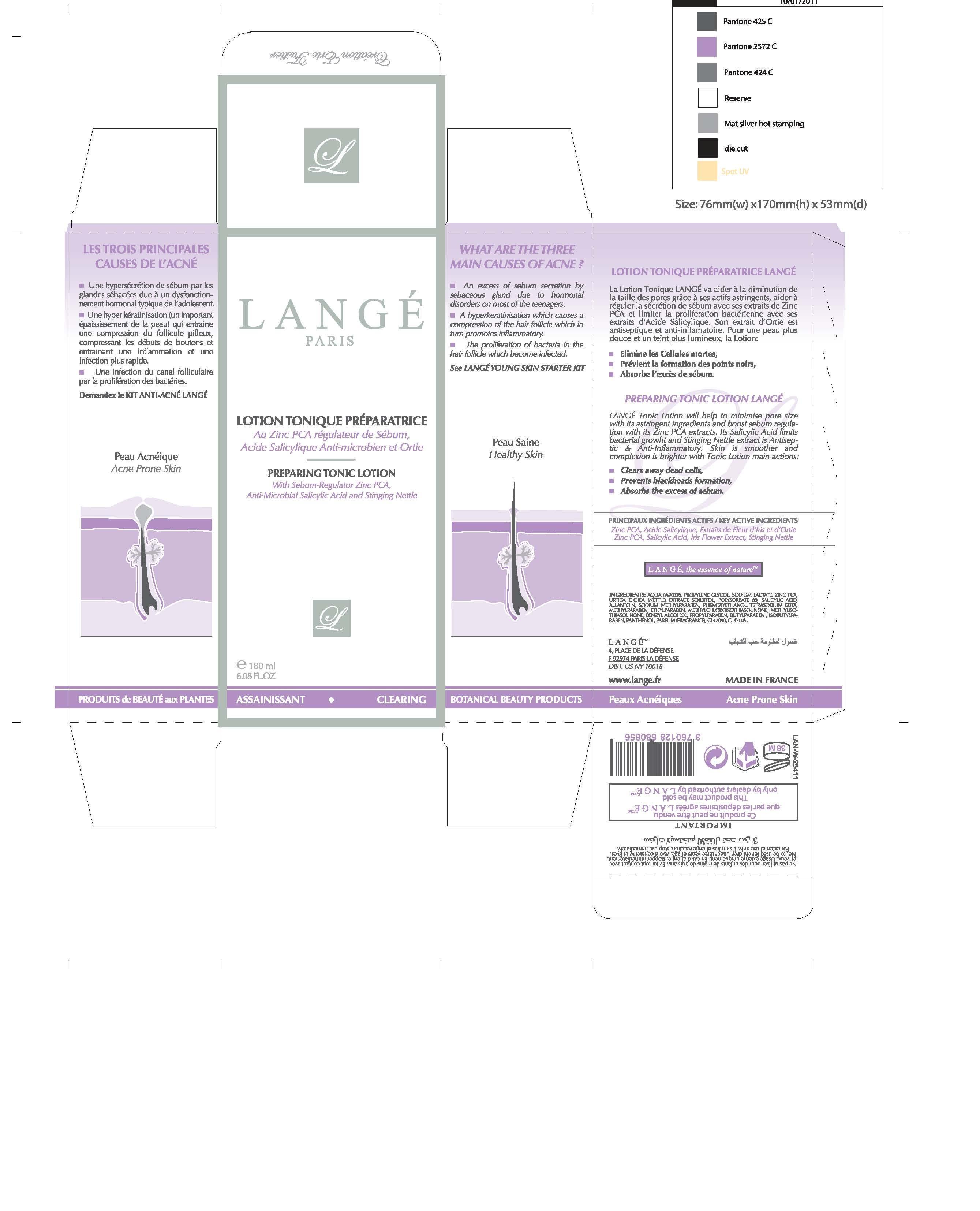 DRUG LABEL: Lightening Serum
NDC: 51830-022 | Form: CREAM
Manufacturer: Lange SAS
Category: otc | Type: HUMAN OTC DRUG LABEL
Date: 20130212

ACTIVE INGREDIENTS: CYCLOMETHICONE 5 0.35 mg/20 mg
INACTIVE INGREDIENTS: WATER; POLYETHYLENE GLYCOL 400; MANNITOL; SODIUM POLYACRYLATE (2500000 MW); DICAPRYLYL ETHER; PROPYLENE GLYCOL; GLYCERIN; PHENOXYETHANOL; SODIUM PYRROLIDONE CARBOXYLATE; PROPYLPARABEN; SODIUM GLUCONATE; EDETATE DISODIUM; METHYLPARABEN; MAGNESIUM ASCORBYL PHOSPHATE; O-CYMEN-5-OL; ETHYLPARABEN; CITRIC ACID MONOHYDRATE; SODIUM CITRATE; TOCOPHEROL; TANGERINE; BUTYLENE GLYCOL; WALTHERIA INDICA LEAF; ENOXOLONE; BAMBUSA VULGARIS TOP; ASCOPHYLLUM NODOSUM; ICODEXTRIN; FERULIC ACID; GLYCYRRHIZA GLABRA; MALIC ACID; TARTARIC ACID; FREESIA ALBA FLOWER; GARDENIA TAITENSIS FLOWER; HIBISCUS SABDARIFFA FLOWER; LILIUM CANDIDUM FLOWER

KEY ACTIVE INGREDIENTS

Seaweed, Licorice Root and Pearl Protein Extracts

PURPOSE

LIGHTENING SERUM

Coup d'eclat with Seaweed extract and Pearl Protein

Keep out of reach of children.

INDICATIONS AND USAGE

LIGHTENING SERUM LANGE
Coup d'eclat Serum is an intensive booster treatment, highly concentrated with whitening Complex. This soft and melting light-gel feel ultra-modern formula will help to: correct skin pigmentation to create a more even appearance, improve skin tone and clarity, creating a more radiant complexion, protect, revitalize, and sublime skin, reinforce action from other LANGE Lightening Products.

WARNING!
Avoid contact with the eyes; avoid or afford protecting from UV whilst using products containing AHA because of the suggestion of susceptibility to increased damage from UV.

DOSAGE AND ADMINISTRATION

20 ml
0.68 FL. OZ

INACTIVE INGREDIENT

WATER
PEG-8
DICAPRYLYL ETHER
CYCLOPENTASILOXANE
MANNITOL
SODIUM POLYACRYLATE
PROPYLENE GLYCOL
GLYCERIN
PHENOXYETHANOL
C30-45 ALKYL CETEARYL DIMETHICONE CROSSPOLYMER
SODIUM PCA
PROPYLPARABEN
SODIUM GLUCONATE
DISODIUM EDTA
METHYLPARABEN
MAGNESIUM ASCORBYL PHOSPHATE
o-CYMEN-5-OL
ETHYLPARABEN
CITRIC ACID
SODIUM CITRATE
TOCOPHEROL
CITRUS NOBILIS (MANDARIN ORANGE) FRUIT EXTRACT
BUTYLENE GLYCOL
WALTHERIA INDICA LEAF EXTRACT
GLYCYRRHETINIC ACID
BAMBUSA VULGARIS LEAF/STEM EXTRACT
ASCOPHYLLUM NODOSUM EXTRACT
DEXTRIN
FERULIC ACID
GLYCYRRHIZA GLABRA (LICORICE) ROOT EXTRACT
MALIC ACID
HYDROLYZED CONCHIOLIN PROTEIN
TARTARIC ACID
FREESIA ALBA FLOWER EXTRACT
GARDENIA TAHITENSIS FLOWER EXTRACT
HIBISCUS SABDARIFFA FLOWER EXTRACT
LILIUM CANDIDUM FLOWER EXTRACT